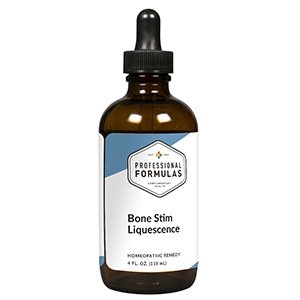 DRUG LABEL: Bone Stim Liquescence
NDC: 63083-3005 | Form: LIQUID
Manufacturer: Professional Complementary Health Formulas
Category: homeopathic | Type: HUMAN OTC DRUG LABEL
Date: 20190815

ACTIVE INGREDIENTS: BOS TAURUS BONE 3 [hp_X]/118 mL; EGG SHELL 3 [hp_X]/118 mL; LETTUCE 3 [hp_X]/118 mL; OSTREA EDULIS SHELL 3 [hp_X]/118 mL; OYSTER SHELL CALCIUM CARBONATE, CRUDE 4 [hp_X]/118 mL; CALCIUM CHLORIDE 4 [hp_X]/118 mL; ANHYDROUS DIBASIC CALCIUM PHOSPHATE 4 [hp_X]/118 mL; CALCIUM SULFATE ANHYDROUS 4 [hp_X]/118 mL; EQUISETUM ARVENSE TOP 4 [hp_X]/118 mL; BLACK WALNUT 4 [hp_X]/118 mL; MAGNESIUM 4 [hp_X]/118 mL; MANGANESE 4 [hp_X]/118 mL; VITAMIN A 4 [hp_X]/118 mL; VITAMIN D 4 [hp_X]/118 mL; ERGOCALCIFEROL 4 [hp_X]/118 mL; LINOLENIC ACID 4 [hp_X]/118 mL; BOS TAURUS BONE MARROW 4 [hp_X]/118 mL; CALCIUM FLUORIDE 6 [hp_X]/118 mL; BEEF KIDNEY 6 [hp_X]/118 mL; BEEF LIVER 6 [hp_X]/118 mL; ENTEROBIUS VERMICULARIS 6 [hp_X]/118 mL; SILICON DIOXIDE 6 [hp_X]/118 mL; CHICKEN SKIN, COOKED 6 [hp_X]/118 mL; THYROID, UNSPECIFIED 6 [hp_X]/118 mL; NICKEL 12 [hp_X]/118 mL
INACTIVE INGREDIENTS: ALCOHOL; WATER

T5

ACTIVE INGREDIENTS

Bone meal 3X
Egg shell 3X
Lactuca sativa 3X
Oyster shell 3X
Calcarea carbonica 4X
Calcarea muriatica 4X
Calcarea phosphorica 4X
Calcarea sulphurica 4X
Equisetum arvense 4X
Juglans nigra 4X
Magnesium metallicum 4X
Manganum metallicum 4X
Vitamin A 4X
Vitamin D 4X
Vitamin D2 4X
Vitamin D3 4X
Vitamin F 4X
Bone 4X, 6X
Calcarea fluorica 6X
Kidney 6X
Liver 6X
Parathyroid 6X
Silicea 6X
Skin 6X
Thyroid 6X
Niccolum metallicum 12X

QUESTIONS

Professional Formulas

PO Box 2034 Lake Oswego, OR 97035

INDICATIONS

For the temporary relief of minor aches and pains in the bones, muscles, or joints, or reduced strength.*

PURPOSE

*Claims based on traditional homeopathic practice, not accepted medical evidence. Not FDA evaluated.

WARNINGS

In case of overdose, get medical help or contact a poison control center right away.

Keep out of the reach of children.

PREGNANCY OR BREAST FEEDING

If pregnant or breastfeeding, ask a healthcare professional before use.

DIRECTIONS

Place drops under tongue 30 minutes before/after meals. Adults and children 12 years and over: Take one full dropper up to 2 times per day. Consult a physician for use in children under 12 years of age.

OTHER INFORMATION

Tamper resistant. If seal is broken, do not use. After opening, close container tightly and store at room temperature away from heat.

INACTIVE INGREDIENTS

20% ethanol, purified water.

LABEL

Est 1985

Professional Formulas

Complementary Health

Bone Stim Liquescence

Homeopathic Remedy

4 FL. OZ. (118 mL)